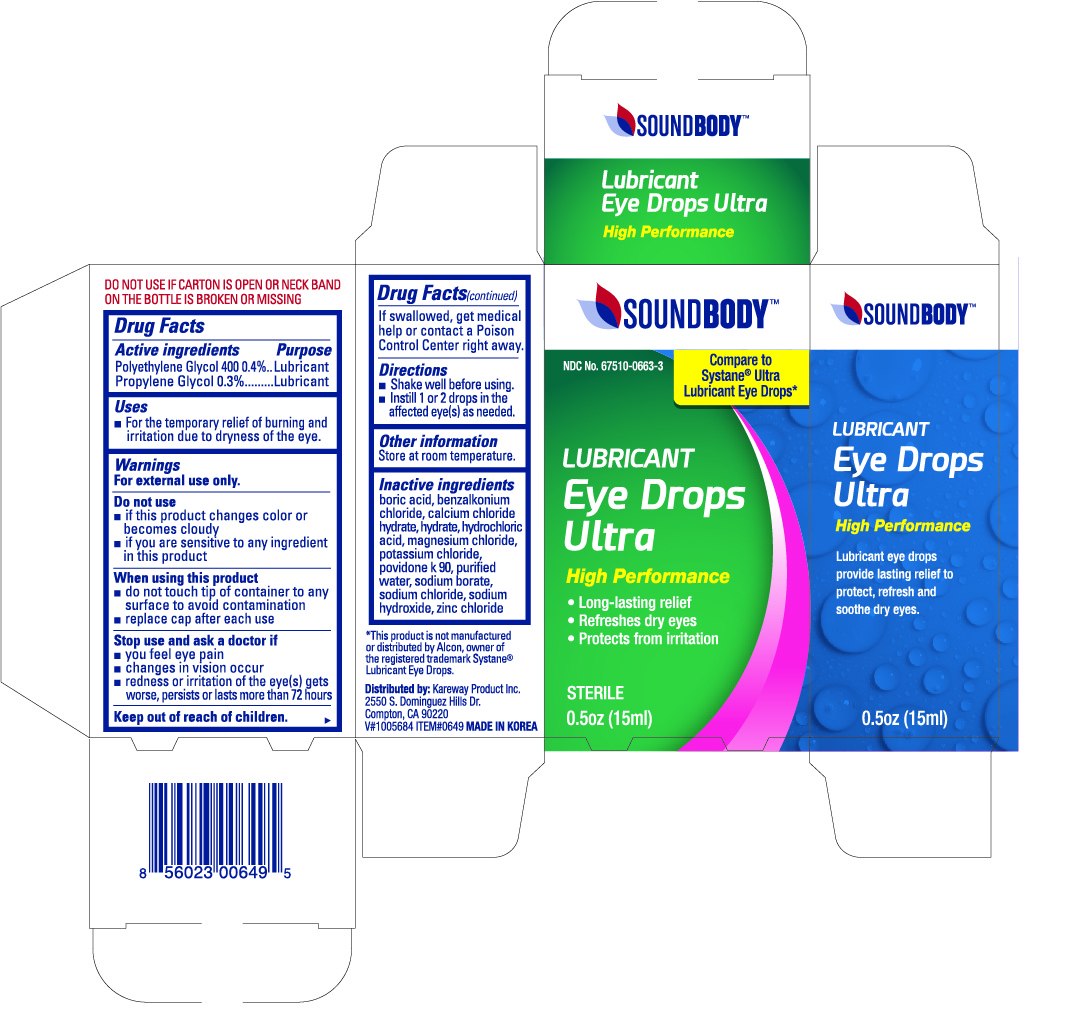 DRUG LABEL: Soundbody Eye Lubricant
NDC: 67510-0649 | Form: LIQUID
Manufacturer: Kareway Product, Inc.
Category: otc | Type: HUMAN OTC DRUG LABEL
Date: 20220708

ACTIVE INGREDIENTS: POLYETHYLENE GLYCOL 400 4 mg/1 mL; PROPYLENE GLYCOL 3 mg/1 mL
INACTIVE INGREDIENTS: BENZALKONIUM CHLORIDE; BORIC ACID; HYDROCHLORIC ACID; POTASSIUM CHLORIDE; WATER; SODIUM CHLORIDE; SODIUM HYDROXIDE

Soundbody Lubricant Eye Drops Ultra

Active ingredients

Polyethylene Glycol 400 0.4%

Propylene Glycol 0.3%

Purpose

Lubricant

Lubricant

Uses

- for the temporary relief of burning and irritation due to dryness of the eye

Warnings

For external use only.

Do not use

- if this product changes color or becomes cloudy
- if you are sensitive to any ingredient in this product

When using this product

- do not touch tip of container to any surface to avoid contamination
- replace cap after each use

Stop use and ask a doctor if

- you feel eye pain
- changes in vision occur
- redness or irritation of the eye(s) gets worse, persists or lasts more than 72 hours

Keep out of reach of children.

If swallowed, get medical help or contact a Poison Control Center right away.

Directions

- Shake well before using.
- Instill 1 or 2 drops in the affected eye(s) as needed.

Other information

Store at room temperature.

Inactive ingredients

benzalkonium chloride, boric acid, hydrochloric acid, hydroxyethyl cellulose, potassium chloride, purified water, sodium chloride, sodium hydroxide

PACKAGE LABEL

Soundbody Lubricant Eye Drops Ultra